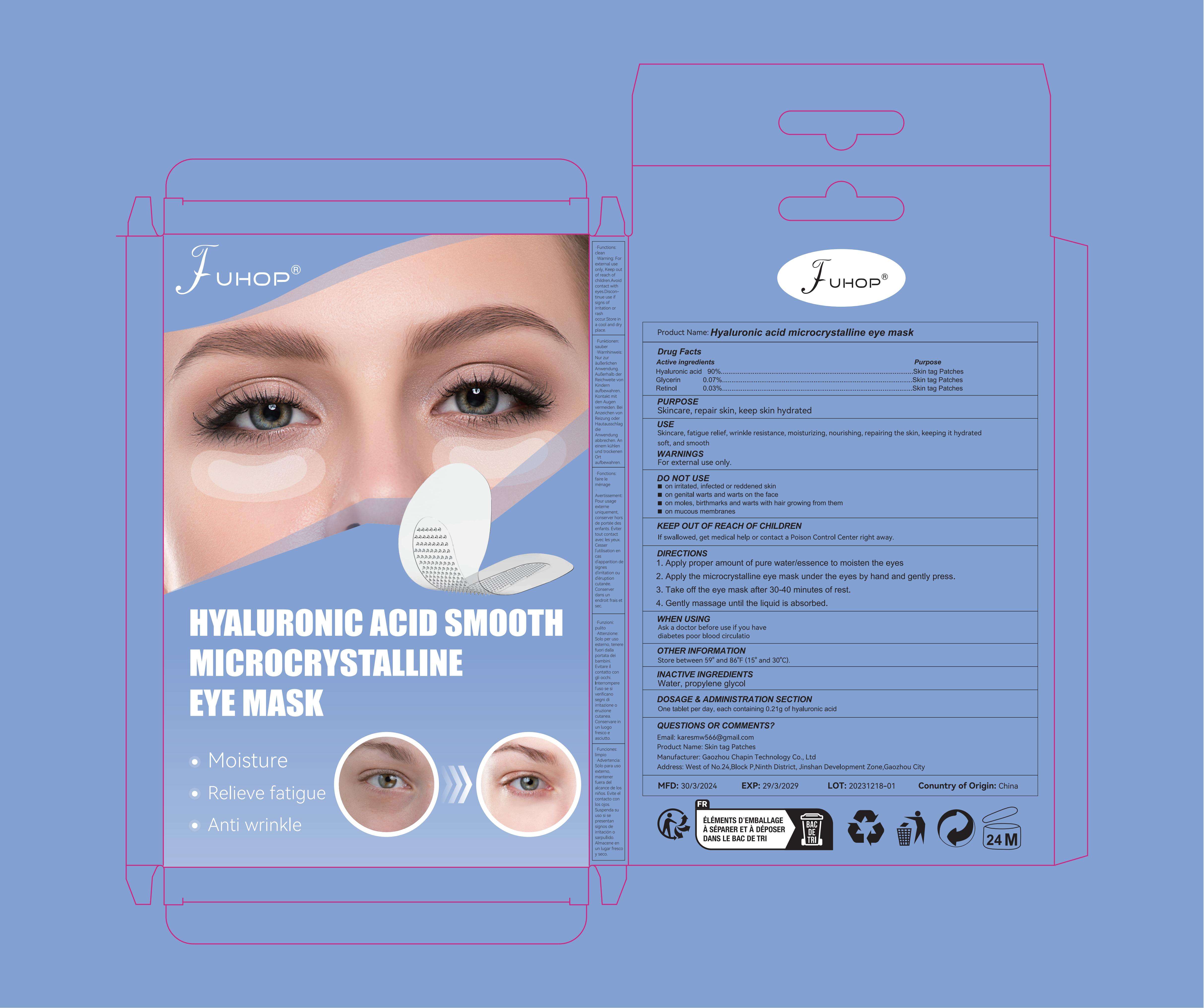 DRUG LABEL: Hyaluronic acid microcrystalline eye mask
NDC: 84168-008 | Form: PATCH
Manufacturer: Gaozhou Chapin Technology Co., Ltd
Category: otc | Type: HUMAN OTC DRUG LABEL
Date: 20240404

ACTIVE INGREDIENTS: HYALURONIC ACID 900 mg/1 g; GLYCERIN 70 mg/1 g; RETINOL 30 mg/1 g
INACTIVE INGREDIENTS: PROPYLENE GLYCOL 1-CAPRATE 10 mg/1 g; WATER 20 mg/1 g

Active ingredients

Hyaluronic acid：90%
Glycerin：0.07%
Retinol：0.03

PURPOSE

Skincare, repair skin, keep skin hydrated

USE

Skincare, fatigue relief, wrinkle resistance, moisturizing, nourishing, repairing the skin, keeping it hydrated
soft, and smooth

WARNINGS

For external use only

DO NOT USE

on irritated, infected or reddened skin
on genital warts and warts on the face
on moles, birthmarks and warts with hair growing from them
on mucous membrane

KEEP OUT OF REACH OF CHILDREN

If swallowed, get medical help or contact a Poison Control Center right away

WHEN USING

Ask a doctor before use if you have
diabetes poor blood circulatio

INACTIVE INGREDIENTS

PROPYLENE GLYCOL,WATER

DOSAGE & ADMINISTRATION SECTION

One tablet per day, each containing 0.21g of hyaluronic acid